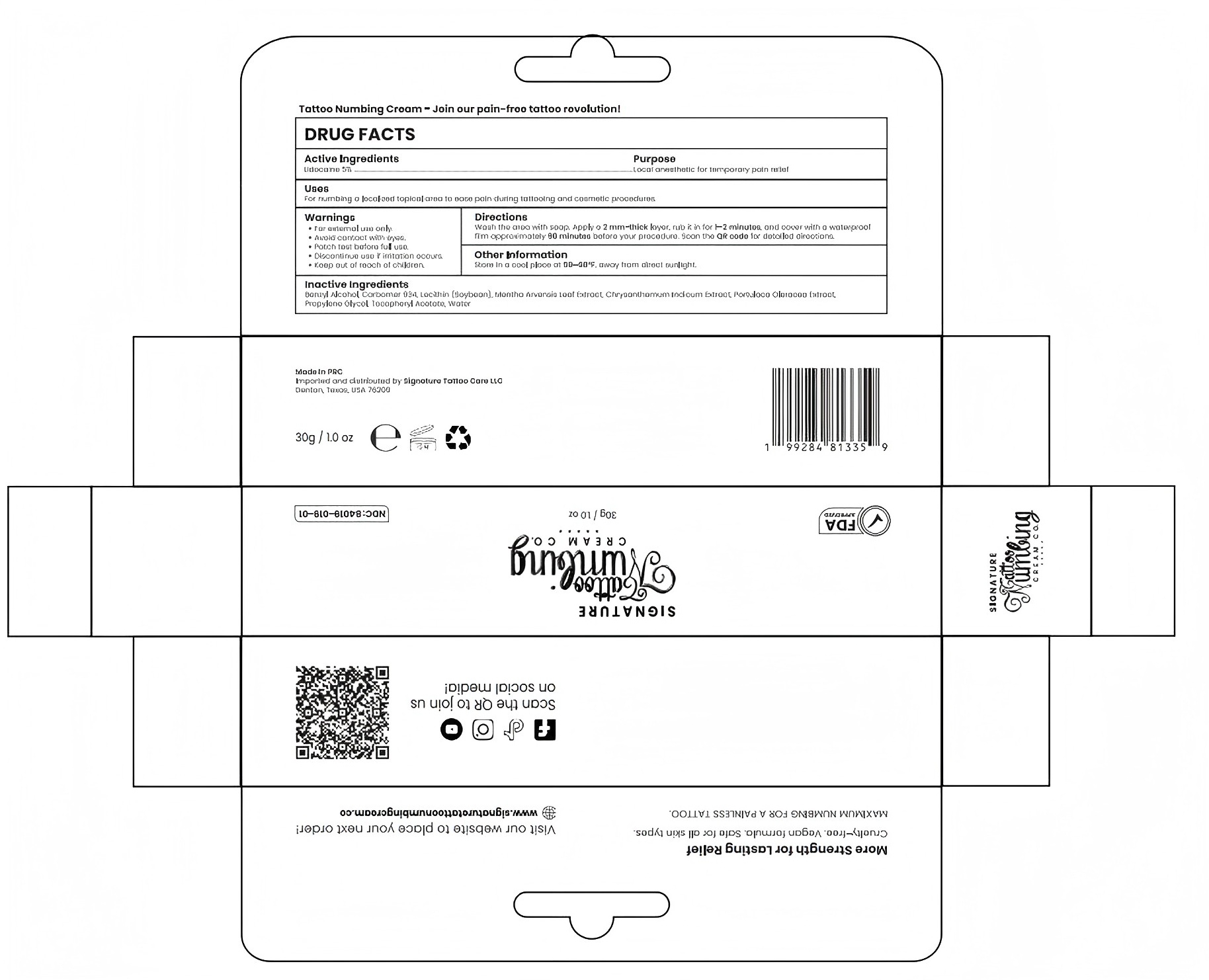 DRUG LABEL: 5% Signature Numb cream
NDC: 84019-029 | Form: CREAM
Manufacturer: Shengnan (Guangzhou) Cosmetics Co., LTD
Category: otc | Type: HUMAN OTC DRUG LABEL
Date: 20250310

ACTIVE INGREDIENTS: LIDOCAINE 100 mg/1 g
INACTIVE INGREDIENTS: BENZYL ALCOHOL; WATER; CARBOMER 934; LECITHIN, SOYBEAN

Stop use and consulta doctor if an allergicreaction occurs.
Keep out of reach of children.

PURPOSE

Used for numbing local area prior to tattooing

STOP USE

Discontinueuse if signs of irritation or rash occur

ACTIVE INGREDIENT

5% Lidocaine

WHEN USING

Wash the area with soap and water.

INACTIVE INGREDIENT

Benzyl Alcohol, Carbomer 934, Lecithin(Soybean), Propylene Glycol, Tocopheryl Acetate, Water

DOSAGE AND ADMINISTRATION

Apply 1-3 times a week

INDICATIONS AND USAGE

Apply a 2mm thick layer of cream, rub it in, and cover it with a waterproof film.Leave on for approximately 90 minutes before your procedure for maximum numbing effect.